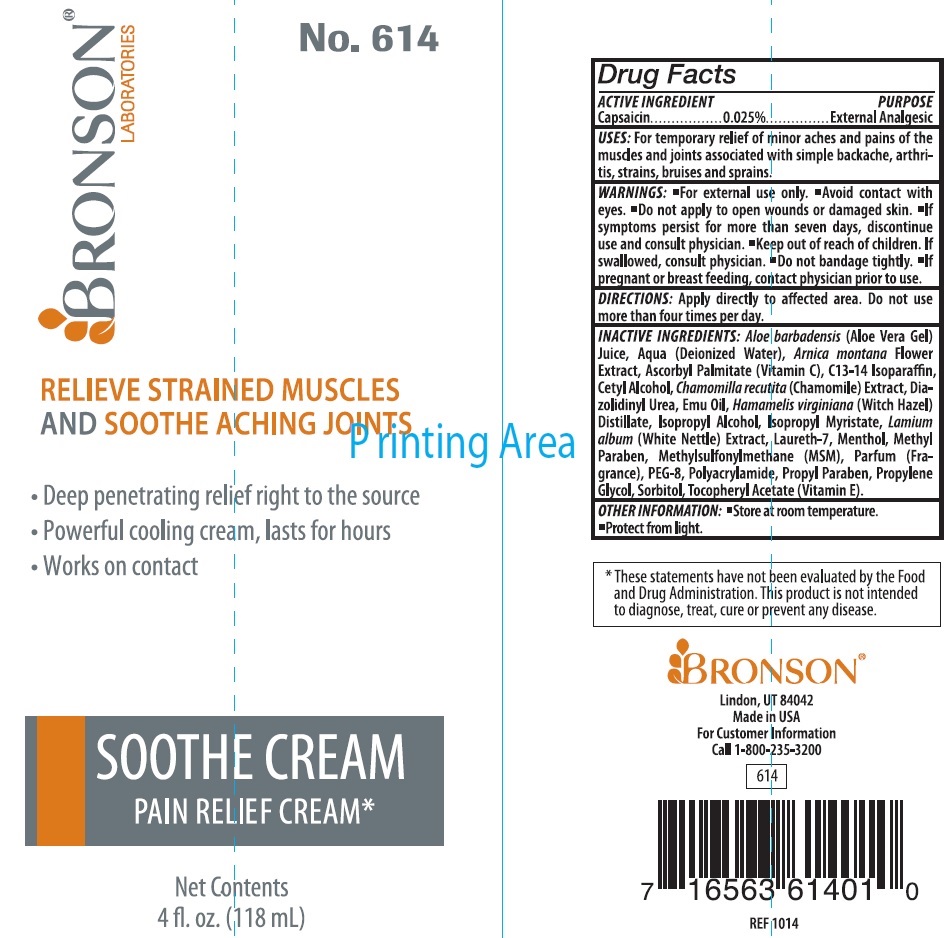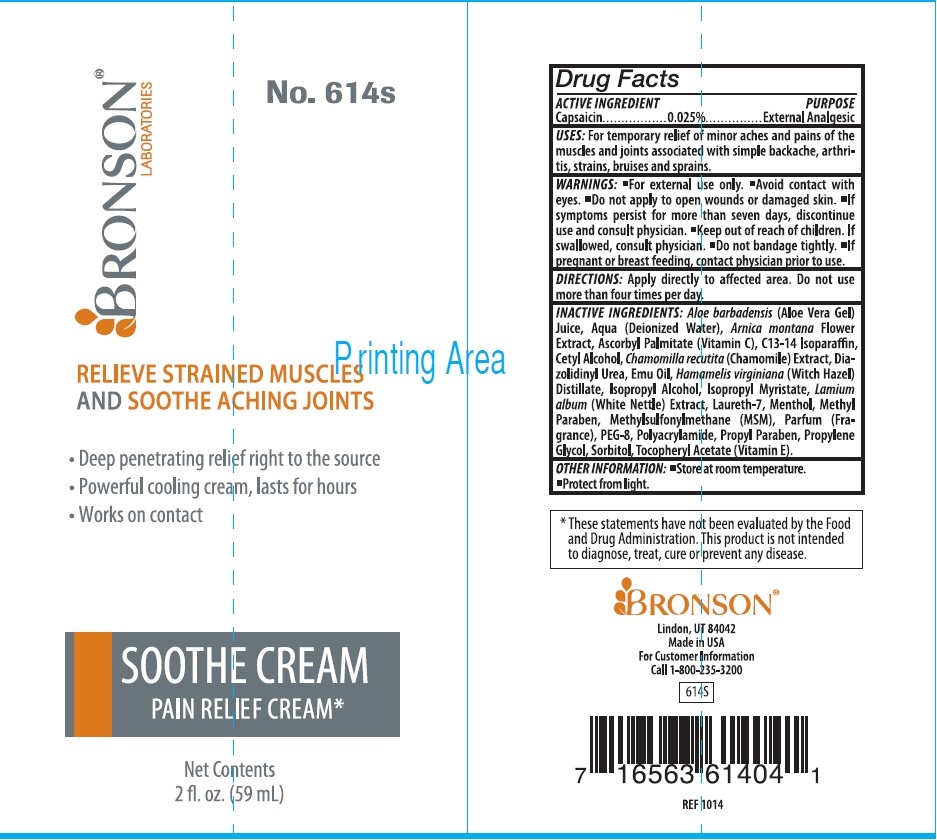 DRUG LABEL: BRONSON SOOTHE Pain Relief
NDC: 83158-387 | Form: CREAM
Manufacturer: BRONSON NUTRITIONALS, LLC
Category: otc | Type: HUMAN OTC DRUG LABEL
Date: 20231106

ACTIVE INGREDIENTS: CAPSAICIN 0.25 mg/1 mL
INACTIVE INGREDIENTS: ALOE VERA LEAF; WATER; ARNICA MONTANA FLOWER; ASCORBYL PALMITATE; C13-14 ISOPARAFFIN; CETYL ALCOHOL; CHAMOMILE; DIAZOLIDINYL UREA; EMU OIL; WITCH HAZEL; ISOPROPYL ALCOHOL; ISOPROPYL MYRISTATE; LAMIUM ALBUM WHOLE; LAURETH-7; MENTHOL; METHYLPARABEN; DIMETHYL SULFONE; POLYETHYLENE GLYCOL 400; PROPYLPARABEN; PROPYLENE GLYCOL; SORBITOL; .ALPHA.-TOCOPHEROL ACETATE

BRONSON SOOTHE CREAM Pain Relief Cream

ACTIVE INGREDIENT

Capsaicin 0.025%

PURPOSE

External Analgesic

USES:

For temporary relief of minor aches and pains of the muscles and joints associted with simple backache, arthritis, strains, bruises and sprains.

WARNINGS

- For external use only.
- Avoid contact with eyes.
- Do not apply to open wounds or damaged skin.
- If symtoms persist for more than seven days, discontinue use and consult physician.

Keep out of reach of children.

- If swallowed, contact physician.
- Do not bandage tightly .
- If pregnant or breast feeding, contact physician prior to use.

DIRECTIONS:

Apply directly to affected area. Do not use more than four times per day.

INACTIVE INGREDIENTS:

Aloe barbadensis (Aloe Vera Gel) Juice, Aqua (Deionized Water), Arnica montana Flower Extract, Ascorbyl Palmitate (Vitamin C), C13-14 Isoparaffin, Cetyl Alcohol, Chamomilla recutita (Chamomile) Extract, Diazolidinyl Urea, Emu Oil, Hamamelis virginiana (Witch Hazel) Distillate, Isopropyl Alcohol, Isopropyl Myristate, Lamium album (White Nettle) Extract, Laureth-7, Menthol, Methyl Paraben, Methylsulfonylmethane (MSM), Parfum (Fragrance), PEG-8, Polyacrylamide, Propyl Paraben, Propylene Glycol, Sorbitol, Tocopheryl Acetate (Vitamin E).

OTHER INFORMATION:

- Store at room temperature.
- Protect from light.